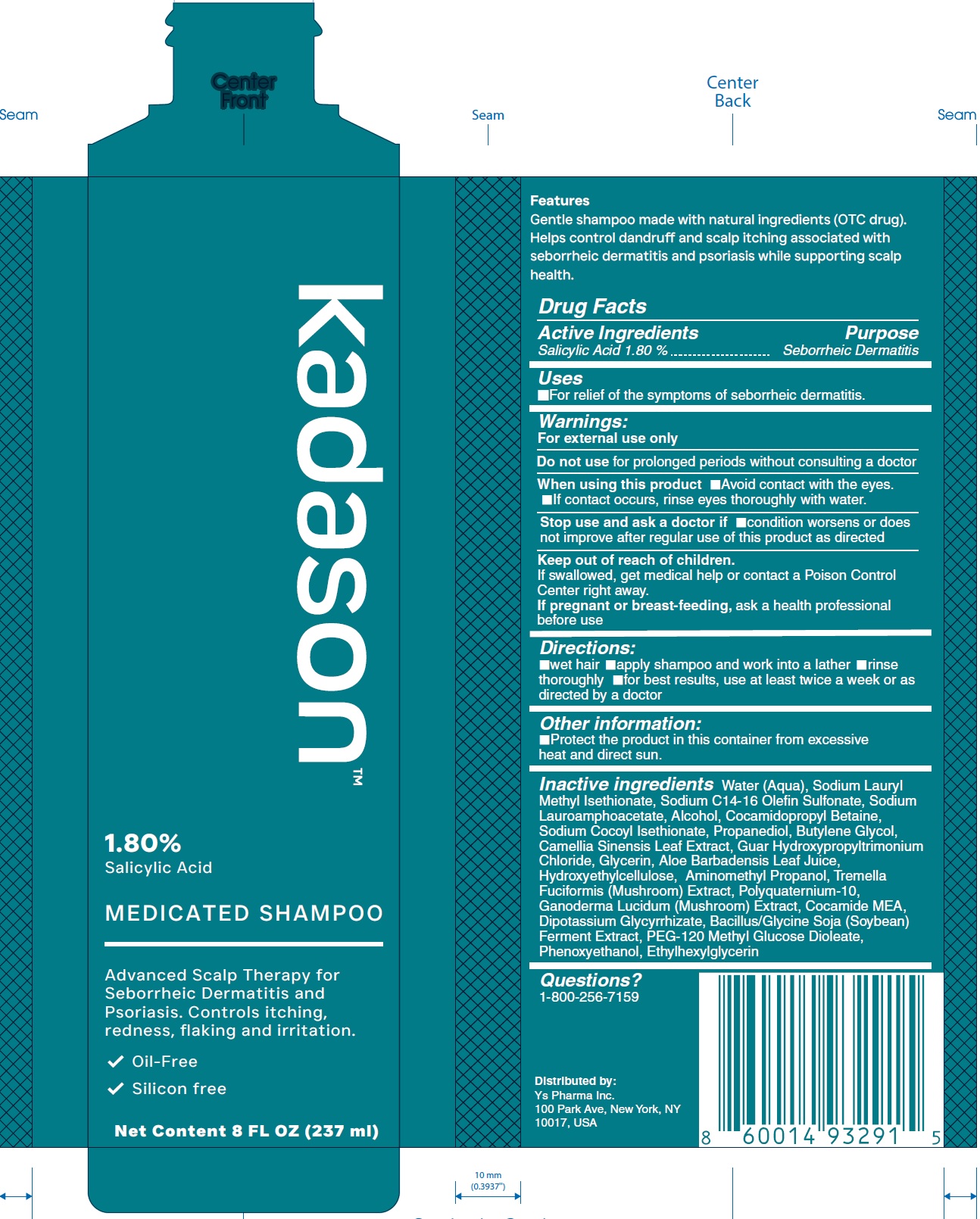 DRUG LABEL: Kadason Medicated
NDC: 87263-927 | Form: SHAMPOO
Manufacturer: Ys Pharma Inc.
Category: otc | Type: HUMAN OTC DRUG LABEL
Date: 20251210

ACTIVE INGREDIENTS: SALICYLIC ACID 18 mg/1 mL
INACTIVE INGREDIENTS: WATER; SODIUM LAUROYL METHYL ISETHIONATE; SODIUM C14-16 OLEFIN SULFONATE; SODIUM LAUROAMPHOACETATE; ALCOHOL; COCAMIDOPROPYL BETAINE; SODIUM COCOYL ISETHIONATE; PROPANEDIOL; BUTYLENE GLYCOL; GREEN TEA LEAF; GUAR HYDROXYPROPYLTRIMONIUM CHLORIDE; GLYCERIN; ALOE VERA LEAF JUICE; HYDROXYETHYLCELLULOSE; AMINOMETHYL PROPANOL; TREMELLA FUCIFORMIS FRUITING BODY; REISHI; COCO MONOETHANOLAMIDE; DIPOTASSIUM GLYCYRRHIZATE; SOYBEAN; PEG-120 METHYL GLUCOSE DIOLEATE; PHENOXYETHANOL; ETHYLHEXYLGLYCERIN

Kadason Medicated Shampoo

Active Ingredients

Salicylic Acid 1.80 %

Purpose

Seborrheic Dermatitis

Uses

- For relief of the symptoms of seborrheic dermatitis.

Warnings:

For external use only

Do not use

for prolonged periods without consulting a doctor

When using this product

- Avoid contact with the eyes.
- If contact occurs, rinse eyes thoroughly with water.

Stop use and ask a doctor if

condition worsens or does not improve after regular use of this product as directed

Keep out of reach of children.

If swallowed, get medical help or contact a Poison Control Center right away.

If pregnant or breast-feeding,

ask a health professional before use

Directions:

- wet hair
- apply shampoo and work into a lather
- rinse thoroughly
- for best results, use at least twice a week or as directed by a doctor

Other information:

- Protect the product in this container from excessive heat and direct sun.

Inactive ingredients

Water (Aqua), Sodium Lauryl Methyl Isethionate, Sodium C14-16 Olefin Sulfonate, Sodium Lauroamphoacetate, Alcohol, Cocamidopropyl Betaine, Sodium Cocoyl Isethionate, Propanediol, Butylene Glycol, Camellia Sinensis Leaf Extract, Guar Hydroxypropyltrimonium Chloride, Glycerin, Aloe Barbadensis Leaf Juice, Hydroxyethylcellulose, Aminomethyl Propanol, Tremella Fuciformis (Mushroom) Extract, Polyquaternium-10, Ganoderma Lucidum (Mushroom) Extract, Cocamide MEA, Dipotassium Glycyrrhizate, Bacillus/Glycine Soja (Soybean) Ferment Extract, PEG-120 Methyl Glucose Dioleate, Phenoxyethanol, Ethylhexylglycerin

Questions?

1-800-256-7159